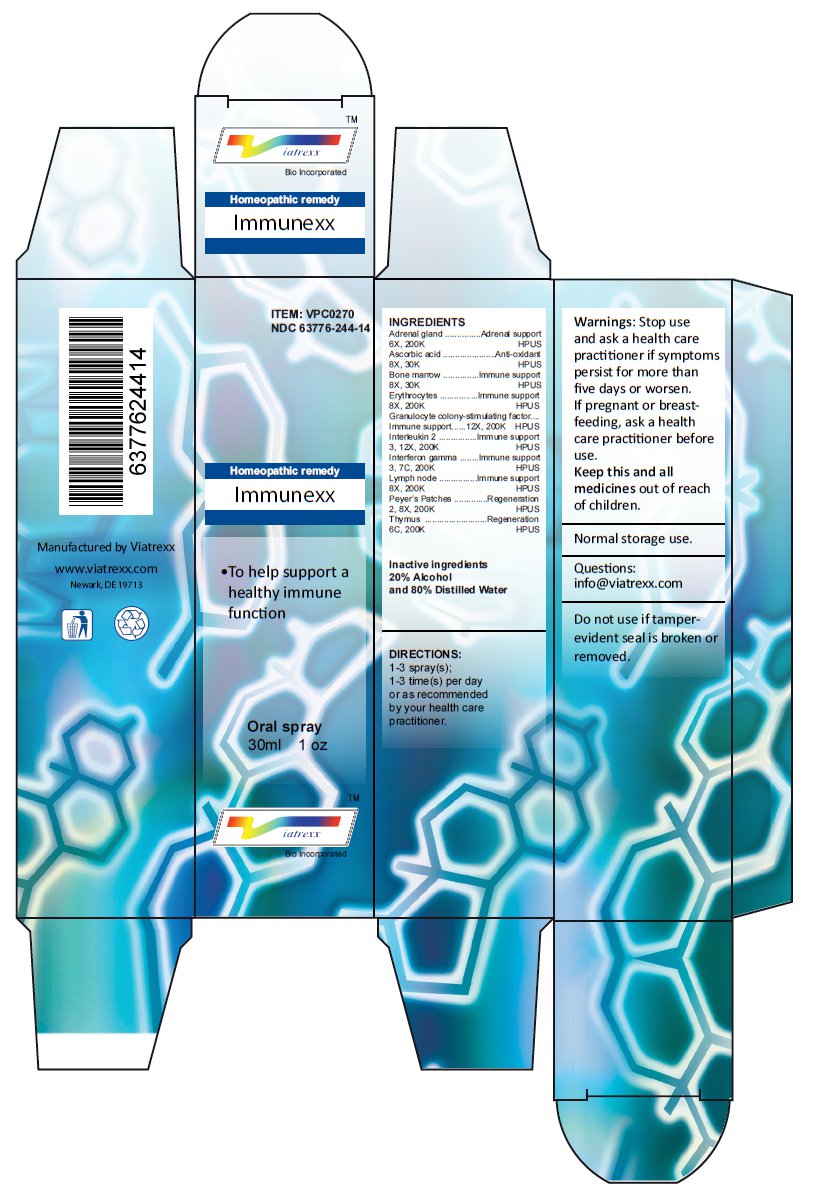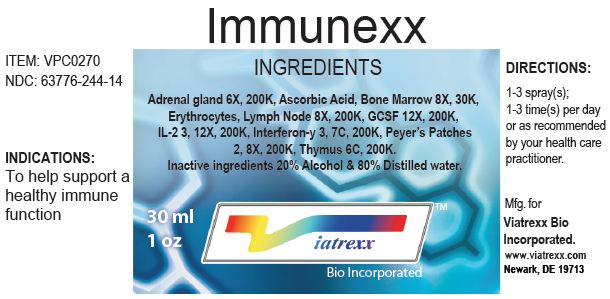 DRUG LABEL: Immunexx
NDC: 63776-244 | Form: SPRAY
Manufacturer: VIATREXX BIO INCORPORATED
Category: homeopathic | Type: HUMAN OTC DRUG LABEL
Date: 20221130

ACTIVE INGREDIENTS: BOS TAURUS ADRENAL GLAND 200 [kp_C]/1 mL; SUS SCROFA ADRENAL GLAND 200 [kp_C]/1 mL; ASCORBIC ACID 30 [kp_C]/1 mL; BOS TAURUS BONE MARROW 30 [kp_C]/1 mL; SUS SCROFA BONE MARROW 30 [kp_C]/1 mL; BOS TAURUS RED BLOOD CELL 200 [kp_C]/1 mL; SUS SCROFA RED BLOOD CELL 200 [kp_C]/1 mL; FILGRASTIM 200 [kp_C]/1 mL; ALDESLEUKIN 200 [kp_C]/1 mL; INTERFERON GAMMA-1A 200 [kp_C]/1 mL; BOS TAURUS LYMPH 200 [kp_C]/1 mL; SUS SCROFA LYMPH 200 [kp_C]/1 mL; BOS TAURUS PEYER'S PATCH 200 [kp_C]/1 mL; SUS SCROFA PEYER'S PATCH 200 [kp_C]/1 mL; BOS TAURUS THYMUS 200 [kp_C]/1 mL; SUS SCROFA THYMUS 200 [kp_C]/1 mL
INACTIVE INGREDIENTS: ALCOHOL; WATER

Immunexx

Active Ingredients

Adrenal gland 6X 200K, Ascorbic acid 8X 30K, Bone marrow 8X 30K, Erythrocytes 8X 200K, Granulocyte colony-stimulating factor 12X 200K, Interleukin 2 3 12X 200K, Interferon gamma 3 7C, 200K, Lymph node 8X 200K, Peyer's Patches 2 8X 200K, Thymus 6C 200K

Purpose:

Adrenal gland | Adrenal support
Ascorbic acid | Anti-oxidant
Bone marrow | Immune support
Erythrocytes | Immune support
Granulocyte colony-stimulating factor | Immune support
Interleukin 2 | Immune support
Interferon gamma | Immune support
Lymph node | Immune support
Peyer's Patches | Regeneration
Thymus | Regeneration

Uses

To help support a healthy immune function

Warnings

Stop use and ask a health care practitioner if symptoms persist for more than five days or worsen. If pregnant or breastfeeding, ask a health care practitioner before use.

Dosage

1-3 spray(s); 1-3 time(s) per day or as recommended by your health care practitioner.

KEEP OUT OF REACH OF CHILDREN

Keep this and all medicines out of reach of children.

Other Ingredients

Alcohol and Water

Other Information

Normal storage use.
Do not use if tamper-evident seal is broken or removed.

Questions

info@viatrexx.com

Principal Display Panel

ITEM: VPC0270
NDC 63776-244-14
Homeopathic remedy
Immunexx
• To help support a healthy immune function
Oral spray
30ml 1 oz
Viatrexx™ Bio Incorporated
Manufactured by Viatrexx
www.viatrexx.com
Newark, DE 19713

Immunexx
30 mL
1 oz
Viatrexx™ Bio Incorporated
ITEM: VPC0270
NDC: 63776-244-14
INDICATIONS:
To help support a healthy immune function
DIRECTIONS:
1-3 spray(s); 1-3 time(s) per day or as recommended by your health care practitioner.
Mfg. for
Viatrexx Bio Incorporated.
www.viatrexx.com
Newark, DE 19713